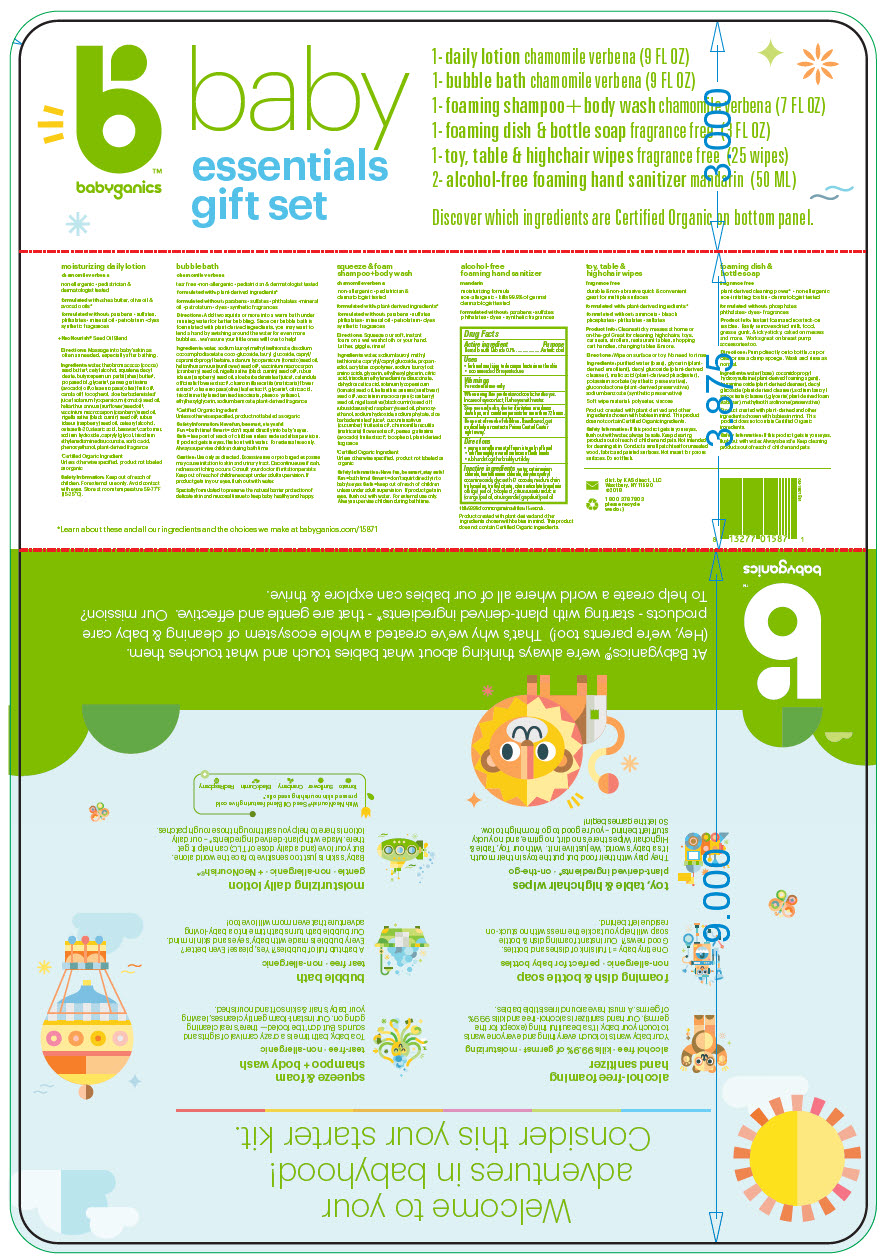 DRUG LABEL: baby essentials gift set
NDC: 59062-5000 | Form: KIT | Route: TOPICAL
Manufacturer: KAS Direct LLC dba BabyGanics
Category: otc | Type: HUMAN OTC DRUG LABEL
Date: 20201104

ACTIVE INGREDIENTS: BENZALKONIUM CHLORIDE 0.1 mg/1 mL
INACTIVE INGREDIENTS: water; cetrimonium chloride; laurtrimonium chloride; dihydroxyethyl cocamine oxide; glycereth-17 cocoate; MEDIUM-CHAIN TRIGLYCERIDES; triethyl citrate; TANGERINE; tocopherol; ORANGE OIL; CITRUS MAXIMA FRUIT RIND OIL

baby essentials gift set

Drug Facts

Active ingredient

Benzalkonium Chloride 0.1%

Purpose

Antimicrobial

Uses

- for hand sanitizing to decrease bacteria on the skin
- recommended for repeated use

Warnings

For external use only

When using this product avoid contact with eyes. In case of eye contact, ﬂush eyes with water.

Stop use and ask a doctor if irritation or redness develops, or if condition persists for more than 72 hours.

Keep out of reach of children. If swallowed, get medical help or contact a Poison Control Center right away.

Directions

- pump a small amount of foam into palm of hand
- rub thoroughly over all surfaces of both hands
- rub hands together briskly until dry

Inactive ingredients

water, cetrimonium chloride, laurtrimonium chloride, dihydroxyethyl cocamine oxide, glycereth-17 cocoate, medium chain triglycerides, triethyl citrate, citrus reticulata (mandarin orange) peel oil, tocopherol, citrus aurantium dulcis (orange) peel oil, citrus grandis (grapefruit) peel oil

dist. by KAS direct, LLC
Westbury, NY 11590

PRINCIPAL DISPLAY PANEL - Kit Package

babyganics

baby
essentials
gift set

1- daily lotion chamomile verbena (9 FL OZ)
1- bubble bath chamomile verbena (9 FL OZ)
1- foaming shampoo+body wash chamomile verbena (7 FL OZ)
1- foaming dish & bottle soap fragrance free (3 FL OZ)
1- toy, table & highchair wipes fragrance free (25 wipes)
2- alcohol-free foaming hand sanitizer mandarin (50 ML)

Discover which ingredients are Certified Organic on bottom panel.